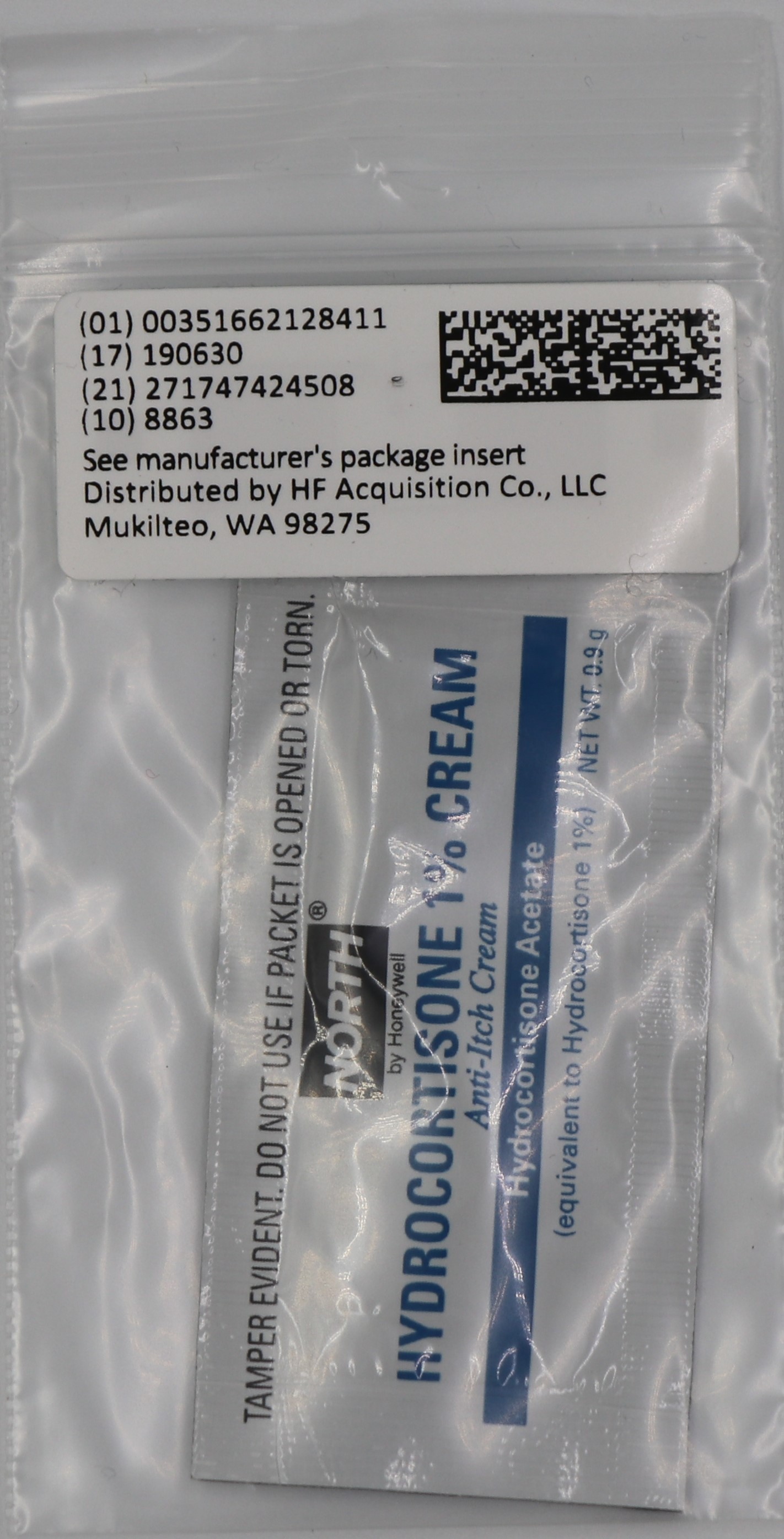 DRUG LABEL: HYDROCORTISONE
NDC: 51662-1284 | Form: OINTMENT
Manufacturer: HF Acquisition Co LLC, DBA HealthFirst
Category: otc | Type: HUMAN OTC DRUG LABEL
Date: 20250805

ACTIVE INGREDIENTS: HYDROCORTISONE ACETATE 1 g/100 g
INACTIVE INGREDIENTS: STEARIC ACID; DIAZOLIDINYL UREA; LIGHT MINERAL OIL; PROPYLPARABEN; WATER; GLYCERIN; EDETATE DISODIUM; POLYETHYLENE GLYCOL, UNSPECIFIED; METHYLPARABEN; PROPYLENE GLYCOL; CETYL ALCOHOL; GLYCERYL MONOSTEARATE; TROLAMINE

ACTIVE INGREDIENT

Hydrocortisone acetate (equivalent to Hydrocortisone 1%)

PURPOSE

Anti-itch cream

DOSAGE AND ADMINISTRATION

for the temporary relief of itching associated with minor skin irritations and rashes
other uses of this product should be only under the advice and supervision of a doctor

WARNINGS

For external use only

Do not use

for the treatment of diaper rash. Consult a doctor

When using this product

avoid contact with eyes
do not begin use of any other hydrocortisone product unless you've consulted a doctor

Stop use and ask a doctor if

condition worsens
symptoms persist more than 7 days
condition clears up and occurs again within a few days

Keep out of the reach of children

If swallowed, get medical help or contact a Poison Control Center right away.

DIRECTIONS

adults and children 2 years of age and older: apply to affected area not more than 3 to 4 times daily
children under 2 years; do not use, consult a doctor

OTHER SAFETY INFORMATION

clean the affected area
store at room temperature
do not use any opened or torn packets
you may report a serious adverse reaction to this product to 800-275-3433

INACTIVE INGREDIENT

cetyl alcohol, citric acid, diazolidinyl urea, edetate disodium, glycerin, glyceryl monostearate, methylparaben, mineral oil, polyethylene glycol, propylene glycol, propylparaben, stearic acid, trolamine, water

HOW SUPPLIED

2packs in 1pouch NDC (51662-1284-1)

INDICATIONS AND USAGE

Anti-itch ointment